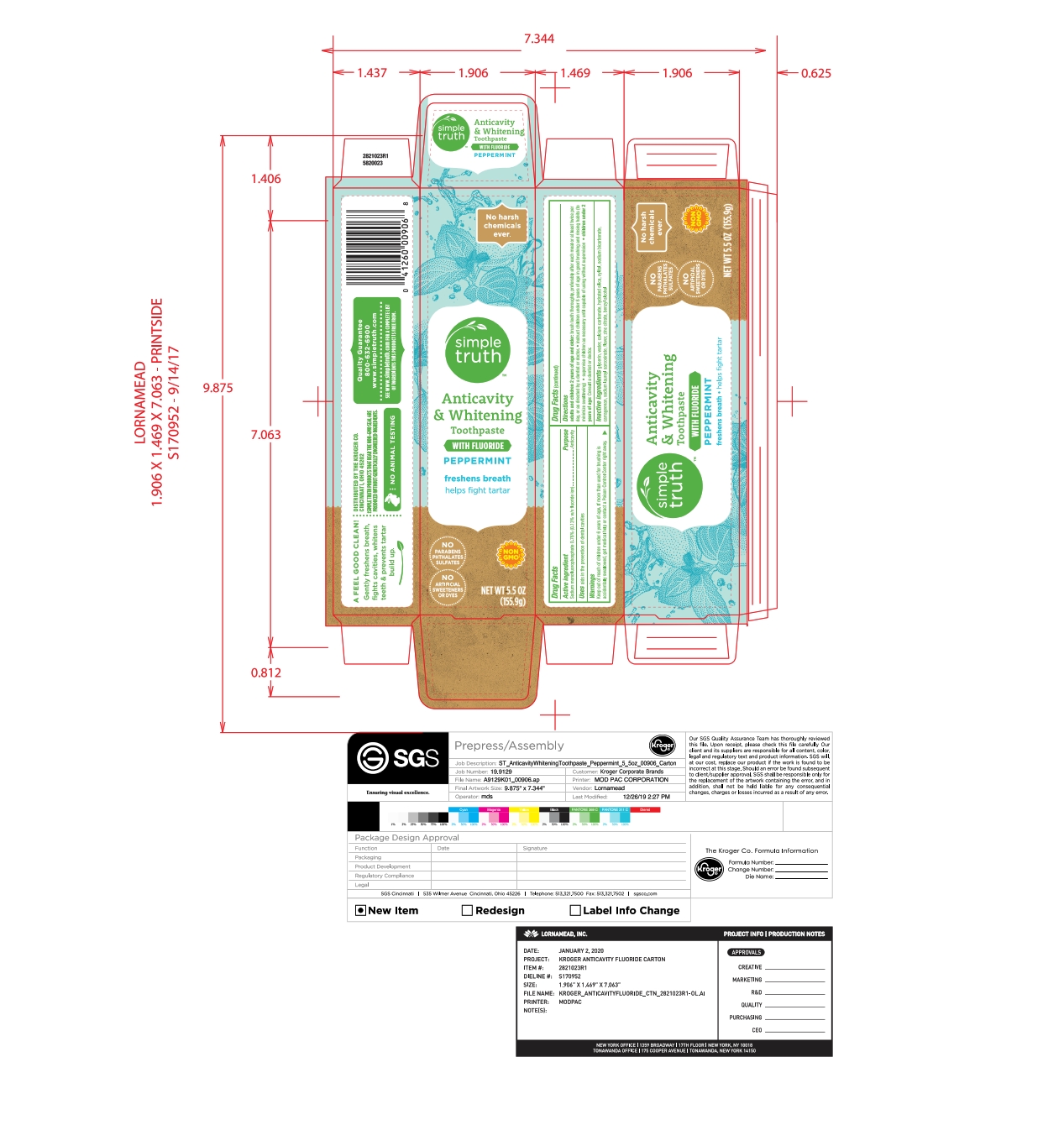 DRUG LABEL: Natural Adult Fluoride
NDC: 30142-223 | Form: PASTE
Manufacturer: Kroger
Category: otc | Type: HUMAN OTC DRUG LABEL
Date: 20251215

ACTIVE INGREDIENTS: SODIUM MONOFLUOROPHOSPHATE 0.76 g/100 g
INACTIVE INGREDIENTS: CARRAGEENAN; GLYCERIN; SODIUM LAUROYL SARCOSINATE; WATER; XYLITOL; ZINC CITRATE; SODIUM BICARBONATE; CALCIUM CARBONATE; HYDRATED SILICA; BENZYL ALCOHOL

5820023 Natural Adult Fluoride

Active ingredient Purpose

Sodium monofluorophosphate 0/76% (0.13% w/v fluoride ion) . . . Anticavity

PURPOSE

Uses

aids in the prevention of dental cavities

WARNINGS

Keep out of reach of children under 6 years of age. If more than is swallowed for brushing si accidentally swallowed, get medical help or contact a Poison Control Center right away.

Directions

adults and children 2 years of age and older: brush teeth thoroughly, preferably after each meal or at least twice per day, or as directed by a dentist or doctor. * instruct children under 6 years of age in good brushing and rinsing habits (to minimize swallowing) * supervise children as necessary until capable of using without supervision * children under 2 years of age: Consult a dentist or doctor.

INACTIVE INGREDIENT

glycerin, water, calcium carbonate, hydrated silica, xylitol, sodium bicarbonate, carrageenan, sodium lauroyl sarcosinate, flavor, zinc citrate, benzyl alcohol